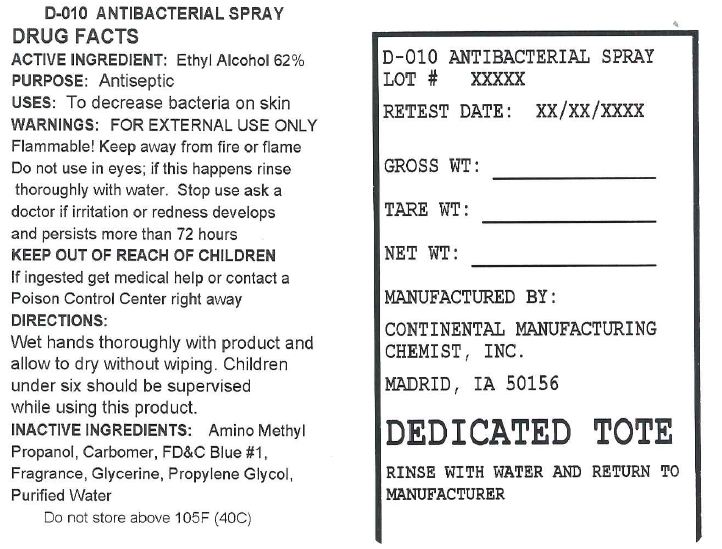 DRUG LABEL: Antibacterial
NDC: 49794-010 | Form: LIQUID
Manufacturer: Continental Manufacturing Chemist, Inc.
Category: otc | Type: HUMAN OTC DRUG LABEL
Date: 20111229

ACTIVE INGREDIENTS: ALCOHOL 620 g/1.0 L
INACTIVE INGREDIENTS: WATER; 2-ETHYLAMINOETHANOL; CARBOMER COPOLYMER TYPE A (ALLYL PENTAERYTHRITOL CROSSLINKED); FD&C BLUE NO. 1; GLYCERIN; PROPYLENE GLYCOL

Antibacterial

Active ingredient

Ethyl Alcohol 62%

Purpose

Antiseptic

Use(s)

To decrease bacteria on skin

Warnings

For external use only

Flammable! Keep away from fire or flame. Do not use in eyes; if this happens rinse thoroughly with water.

Stop use and ask a doctor if

irritation or redness develops and persists more than 72 hours.

Keep out of reach of children

If ingested get medical help or contact a Poison Control Center right away

Directions

Wet hands thoroughly with product and allow to dry without wiping. Children under six should be supervised when using this product.

Storage

Do not store above 105F (40C)

Inactive ingredients

Amino Methyl Propanol, Carbomer, Propylene Glycol, Purified Water

Principal Display Panel

Antibacterial Spray Labeling